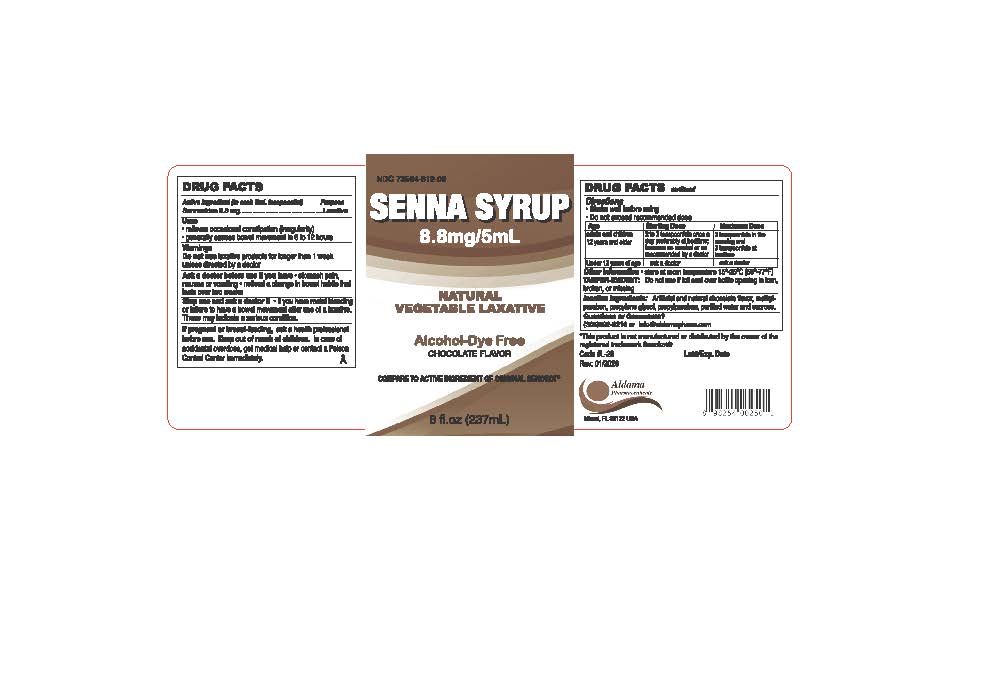 DRUG LABEL: Senna Syrup
NDC: 73564-812 | Form: SOLUTION
Manufacturer: Aldama Pharmaceuticals, Inc
Category: otc | Type: HUMAN OTC DRUG LABEL
Date: 20260123

ACTIVE INGREDIENTS: SENNOSIDES 8.8 mg/5 mL
INACTIVE INGREDIENTS: WATER; SUCROSE; PROPYLENE GLYCOL; METHYLPARABEN; PROPYLPARABEN

Senna Syrup

Active ingredient (in each 5 mL-teaspoonful)

Sennosides 8.8mg

Purpose

Laxative

Uses

- relieves occasional constipation (irregularity)
- generally couses bowel movement in 6 to 12 hours

Warnings

laxative products for longer than 1 week unless directed by a doctor

Do not use

- laxative products for longer than 1 week unless directed by a doctor

Ask a doctor before use if your child

- stomach pain, nauseas or vomiting
- noticed a change in bowel habits that last over two weeks

Stop use and ask a doctor before if

if you have rectal bleeding or failure to have a bowel movement after use of a laxative.

These may indicate serious condition.

If pregnant or breast-feeding

ask a health professional before use

Keep out of reach of children.

In case of accidental overdose, get medical help or contact a Poison Control Center immediately.

Directions

- shake well before using
- Do not exceed recommended dose

Age | Starting Dose | Maximum Dose
adults and children 12 years and older | 2 to 3 teaspoonsfuls once a day preferably at bedtime; increase as needed or as recommended by a doctor | 3 teaspoonfuls in the morning and 3 teaspoonfuls at bedtime
nder 12 years of age | ask a doctor | ask a doctor

Other information

- store at room temperature between 15-30°C (59-86°F)
- TAMPER EVIDENT Do not use if foil seal over bottle opening is torn, broken, or missing

Inactive Ingredient

artificial and natural cherry flavor, citric acid, methylparaben, polyethylene glycol, propylene glycol, propylparaben, purified water, sodium citrate, sucralose

Question or Comments?

call 305-592-9216 or info@aldamapharm.com